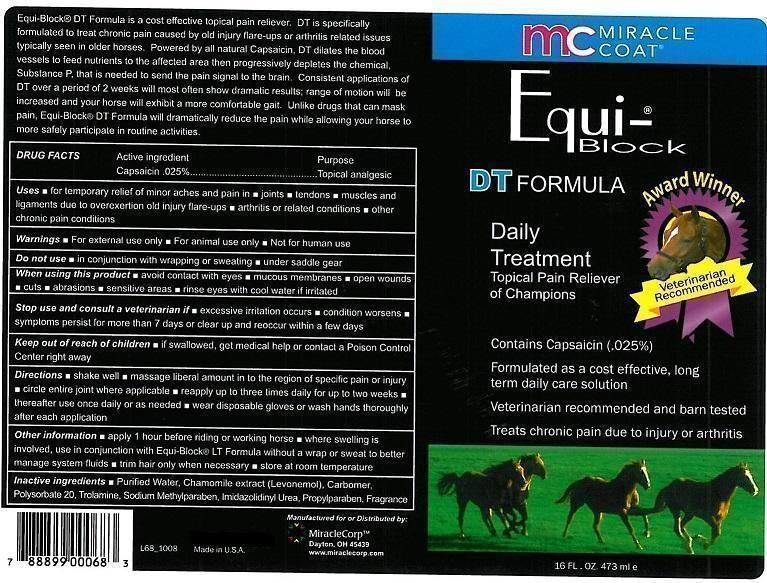 DRUG LABEL: EQUI-BLOCK
NDC: 61429-198 | Form: GEL
Manufacturer: MIRACLE CORP
Category: animal | Type: OTC ANIMAL DRUG LABEL
Date: 20200629

ACTIVE INGREDIENTS: CAPSAICIN 0.025 g/100 mL
INACTIVE INGREDIENTS: WATER; MATRICARIA CHAMOMILLA WHOLE; CARBOMER 940; POLYSORBATE 20; TROLAMINE; METHYLPARABEN SODIUM; IMIDUREA; PROPYLPARABEN

MIRACLE COAT - EQUI-BLOCK DT FORMULA - DAILY TREATMENT

ACTIVE INGREDIENT:

CAPSAICIN .025%

PURPOSE

TOPICAL ANALGESIC

USES

- FOR TEMPORARY RELIEF OF MINOR ACHES AND PAIN IN
- JOINTS
- TENDONS
- MUSCLES AND LIGAMENTS DUE TO OVEREXTENTION OLD INJURY FLARE-UPS
- ARTHRITIS OR RELATED CONDITIONS
- OTHER CHRONIC PAIN CONDITIONS

WARNINGS

- FOR EXTERNAL USE ONLY
- FOR ANIMAL USE ONLY
- NOT FOR HUMAN USE

DO NOT USE

- IN CONJUNCTION WITH WRAPPING OR SWEATING
- UNDER SADDLE GEAR

WHEN USING THIS PRODUCT

- AVOID CONTACT WITH EYES
- MUCOUS MEMBRANES
- OPEN WOUNDS
- CUTS
- ABRASIONS
- SENSITIVE AREAS
- RINSE EYES WITH COOL WATER IF IRRITATED

STOP USE AND CONSULT A VETERINARIAN IF

- EXCESSIVE IRRITATION OCCURS
- CONDITION WORSENS
- SYMPTOMS PERSIST FOR MORE THAN 7 DAYS OR CLEAR UP AND REOCCUR WITHIN A FEW DYS

KEEP OUT OF REACH OF CHILDREN.

- IF SWALLOWED, GET MEDICAL HELP OR CONTACT A POISON CONTROL CENTER RIGHT AWAY.

DIRECTIONS

- SHAKE WELL
- MASSAGE LIBERAL AMOUNT INTO THE REGION OF SPECIFIC PAIN OR INJURY
- CIRCLE ENTIRE JOINT WHERE APPLICABLE
- REAPPLY UP TO THREE TIMES DAILY FOR UP TO TWO WEEKS
- THEREAFTER USE ONCE DAILY OR AS NEEDED
- WEAR DISPOSABLE GLOVES OR WASH HANDS THOROUGHLY AFTER EACH APPLICATION

OTHER INFORMATION

- APPLY 1 HOUR BEFORE RIDING OR WORKING HORSE
- WHERE SWELLING IS INVOLVED, USE IN CONJUNCTION WITH QUI-BLOCKER LT FORMULA WITHOUT A WRAP OR SWEAT TO BETTER MANAGE SYSTEM FLUIDS
- TRIM HAIR ONLY WHEN NECESSARY
- STORE AT ROOM TEMPERATURE

INACTIVE INGREDENTS

- PURIFIED WATER, CHAMOMILE EXTRACT (LEVONEMOL), CARBOMER, POLYSORBATE 20, TROLAMINE, SODIUM METHYLPARABEN, IMIDAZOLIDINYL UREA, PROPYLPARABEN, FRAGRANCE